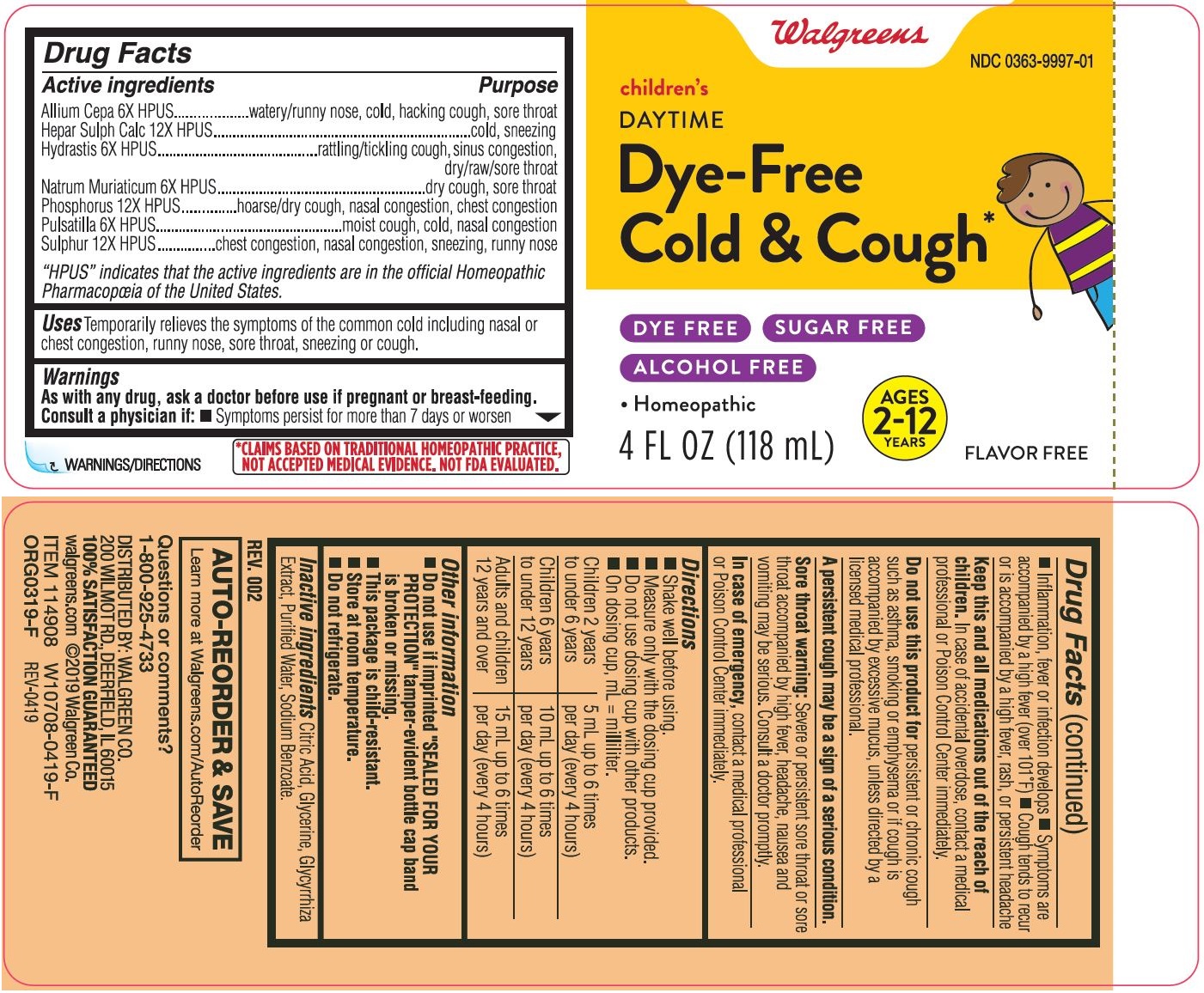 DRUG LABEL: Childrens Cold and Cough
NDC: 0363-9997 | Form: LIQUID
Manufacturer: Walgreen Company
Category: homeopathic | Type: HUMAN OTC DRUG LABEL
Date: 20221215

ACTIVE INGREDIENTS: SULFUR 12 [hp_X]/1 mL; ONION 6 [hp_X]/1 mL; CALCIUM SULFIDE 12 [hp_X]/1 mL; SODIUM CHLORIDE 6 [hp_X]/1 mL; PHOSPHORUS 12 [hp_X]/1 mL; ANEMONE PULSATILLA 6 [hp_X]/1 mL; GOLDENSEAL 6 [hp_X]/1 mL
INACTIVE INGREDIENTS: GLYCYRRHIZA GLABRA; GLYCERIN; CITRIC ACID MONOHYDRATE; WATER; SODIUM BENZOATE

Walgreens Children's Daytime Dye-Free Cold & Cough

Drug Facts

Active ingredients

Allium Cepa 6X HPUS

Hepar Sulph Calc 12X HPUS

Hydrastis 6X HPUS

Natrum Muriaticum 6X HPUS

Phosphorus 12X HPUS

Pulsatilla 6X HPUS

Sulphur 12X HPUS

"HPUS" indicates that the active ingredients are in the official Homeopathic Pharmacoœia of the United States.

Purpose

Allium Cepa 6X HPUS.................watery/runny nose, cold, hacking cough, sore throat

Hepar Sulph Calc 12X HPUS......cold, sneezing

Hydrastis 6X HPUS.....................rattling/tickling cough, sinus congestion, dry/raw/sore throat

Natrum Muriaticum 6X HPUS.....dry cough, sore throat

Phosphorus 12X HPUS..............hoarse/dry cough, nasal congestion, chest congestion

Pulsatilla 6X HPUS.....................moist cough, cold, nasal congestion

Sulphur 12X HPUS.....................chest congestion, nasal congestion, sneezing, runny nose

Uses

Temporarily relieves the symptoms of the common cold including nasal or chest congestion, runny nose, sore throat, sneezing or cough.

Drug Facts (continued)

Warnings

Consult a physician if

- Symptoms persist for more than 7 days or worsen
- Inflammation, fever or infection develops
- Symptoms are accompanied by high fever (101°F)
- Cough tends to recur or is accompanied by high fever, rash or persistent headache

Keep this and all medications out of the reach of children.

In case of accidental overdose, contact a medical professional or Poison Control Center immediately.

Do not use this product for

persistent or chronic cough such as asthma, smoking or emphysema or if cough is accompanied by excessive mucus, unless directed by a licensed medical professional.

Sore throat warning

Severe or persistent sore throat or sore throat accompanied by high fever, headache, nausea and vomiting may be serious. Consult a doctor promptly.

In case of emergency

contact a medical professional or Poison Control Center immediately.

Directions

- Shake well before using.
- Measure only with the dosing cup provided
- Do not use dosing cup with other products
- On dosing cup, mL = milliliter

Children 2 years to; under 6 years | 5 mL up to 6 times; per day (every 4 hours)
Children 6 years to; under 12 years | 10 mL up to 6 times; per day (every 4 hours)
Adults and children 12; years and over | 15 mL up to 6 times; per day (every 4 hours)

Other information

- Do not use if imprinted "SEALED FOR YOUR PROTECTION" tamper-evident bottle cap band is broken or missing.
- This package is child-resistant.
- Store at room temperature.
- Do not refrigerate.

Inactive ingredients

Citric Acid, Glycerine, Glycyrrhiza Extract, Purified Water, Sodium Benzoate.

Questions or Comments?

1-800-925-4733

*CLAIMS BASED ON TRADITIONAL HOMEOPATHIC PRACTICE,

NOT ACCEPTED MEDICAL EVIDENCE. NOT FDA EVALUATED.

Primary Display Panel - 118 mL Bottle Label

Walgreens

NDC 0363-9997-01

children's

DAYTIME

Dye-Free

Cold & Cough

DYE FRE SUGAR FREE

ALCOHOL FREE

- Homeopathic

AGES

2-12

YEARS

FLAVOR FREE

4 FL.OZ. (118 mL)